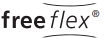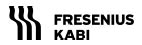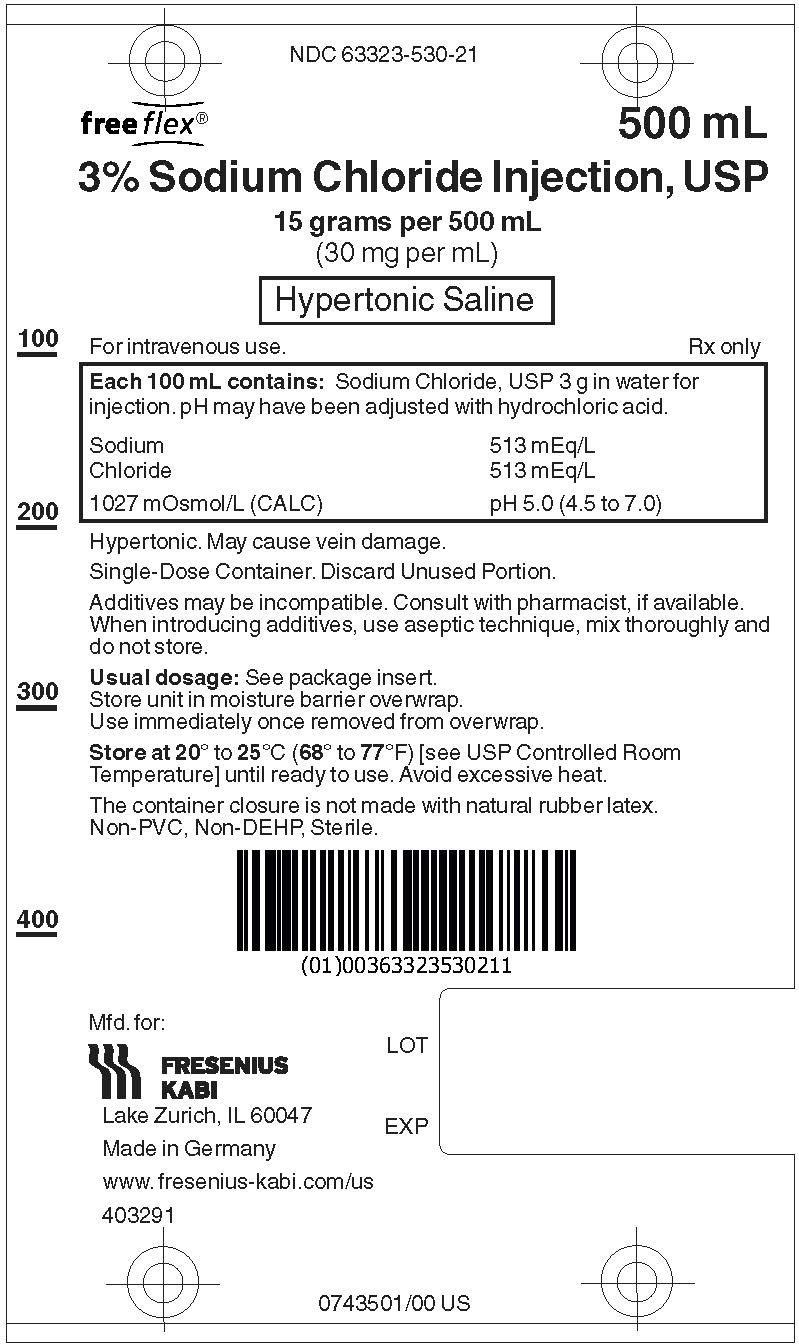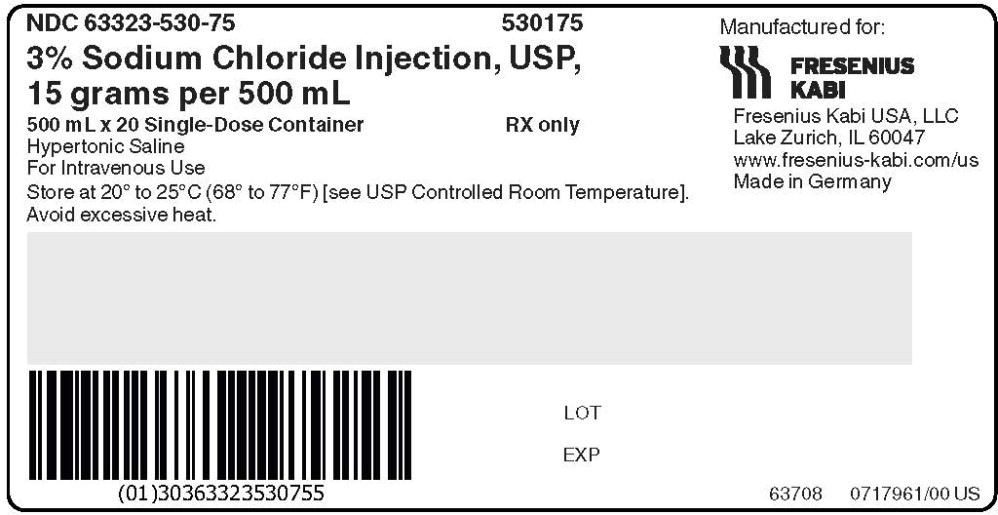 DRUG LABEL: Sodium Chloride
NDC: 63323-530 | Form: INJECTION, SOLUTION
Manufacturer: Fresenius Kabi USA, LLC

Category: prescription | Type: HUMAN PRESCRIPTION DRUG LABEL
Date: 20221024

ACTIVE INGREDIENTS: SODIUM CHLORIDE
 3 g/100 mL
INACTIVE INGREDIENTS: WATER; HYDROCHLORIC ACID

3% Sodium Chloride Injection, USP

Rx only

DESCRIPTION:

3% Sodium Chloride Injection, USP is a sterile, nonpyrogenic, hypertonic solution for fluid and electrolyte replenishment in single dose containers for intravenous administration. The pH may have been adjusted with hydrochloric acid. It contains no antimicrobial agents. Composition, ionic concentration, osmolarity, and pH are shown in Table 1.

Table 1.
 | Size (mL) | Composition (g/L) | Ionic Concentration (mEq/L) |  | *Osmolarity (mOsmol/L) (calc) | pH
 | Size (mL) | Sodium Chloride, USP (NaCl) | Sodium | Chloride | *Osmolarity (mOsmol/L) (calc) | pH
3% Sodium Chloride Injection, USP | 500 | 30 | 513 | 513 | 1,027 | 5.0 (4.5 to 7.0)
*Normal physiological osmolarity range is approximately 280 to 310 mOsmol/L.

The flexible container is fabricated from a specially formulated non-plasticized, film containing polypropylene and thermoplastic elastomers (freeflex® bag). The amount of water that can permeate from the container into the overwrap is insufficient to affect the solution significantly. Solutions in contact with the flexible container can leach out certain of the container's chemical components in very small amounts within the expiration period. The suitability of the container material has been confirmed by tests in animals according to USP biological tests for plastic containers.

CLINICAL PHARMACOLOGY:

3% Sodium Chloride Injection has value as a source of water and electrolytes. It is capable of inducing diuresis depending on the clinical condition of the patient.

INDICATIONS AND USAGE:

3% Sodium Chloride Injection is indicated as a source of water and electrolytes.

CONTRAINDICATIONS:

None known.

WARNINGS:

Hypersensitivity/infusion reactions, including hypotension, pyrexia, tremor, chills, urticaria, rash, and pruritus may occur with 3% Sodium Chloride Injection.

Stop the infusion immediately if signs or symptoms of a hypersensitivity reaction develop, such as tachycardia, chest pain, dyspnea and flushing. Appropriate therapeutic countermeasures must be instituted as clinically indicated.

Depending on the volume and rate of infusion, the intravenous administration of 3% Sodium Chloride Injection can cause fluid and/or solute overloading resulting in dilution of serum electrolyte concentrations, overhydration/hypervolemia, congested states, pulmonary edema, or acid-base imbalance. The risk of dilutive states is inversely proportional to the electrolyte concentration of the injection. The risk of solute overload causing congested states with peripheral and pulmonary edema is directly proportional to the electrolyte concentrations of the injection.

Monitor changes in fluid balance, electrolyte concentrations, and acid base balance during prolonged parenteral therapy or whenever the condition of the patient or the rate of administration warrants such evaluation.

Administer 3% Sodium Chloride Injection with particular caution to patients with or at risk for hypernatremia, hyperchloremia, hypervolemia or with conditions that may cause sodium retention, fluid overload and edema; such as patients with primary hyperaldosteronism, or secondary hyperaldosteronism (for example, associated with hypertension, congestive heart failure, liver disease (including cirrhosis), renal disease (including renal artery stenosis, nephrosclerosis) or pre-eclampsia). Certain medications may increase risk of sodium and fluid retention (see Drug Interactions).

Administer 3% Sodium Chloride Injection with particular caution to patients with severe renal impairment. In such patients administration of Sodium Chloride Injection may result in sodium retention.

PRECAUTIONS:

General

Do not connect flexible plastic containers in series in order to avoid air embolism due to possible residual air contained in the primary container. Such use could result in air embolism due to residual air being drawn from the primary container before administration of the fluid from the secondary container is completed.

Pressurizing intravenous solutions contained in flexible plastic containers to increase flow rates can result in air embolism if the residual air in the container is not fully evacuated prior to administration.

Use of a vented intravenous administration set with the vent in the open position could result in air embolism. Vented intravenous administration sets with the vent in the open position should not be used with flexible plastic containers.

3% Sodium Chloride Injection is hypertonic with an osmolarity of 1,027 mOsmol/L. Administration of hypertonic solutions may cause venous damage and thus should be administered through a large vein, for rapid dilution.

Do not mix or administer 3% Sodium Chloride Injection solution through the same administration set with whole blood or cellular blood components.

Rapid correction of hypo- and hypernatremia is potentially dangerous (risk of serious neurologic complications). Dosage, rate, and duration of administration should be determined by a physician experienced in intravenous fluid therapy.

Drug Interactions

Caution must be exercised in the administration of 3% Sodium Chloride Injection to patients treated with drugs that may increase the risk of sodium and fluid retention, such as corticosteroids.

Caution is advised in patients treated with lithium. Renal sodium and lithium clearance may be increased during the administration of 3% Sodium Chloride Injection. Administration of 3% Sodium Chloride Injection may, therefore, result in decreased lithium levels.

Pregnancy

There are no adequate and well controlled studies with 3% Sodium Chloride Injection in pregnant women and animal reproduction studies have not been conducted with this drug. Therefore, it is not known whether 3% Sodium Chloride Injection can cause fetal harm when administered to a pregnant woman. 3% Sodium Chloride Injection should be given during pregnancy only if the potential benefit justifies the potential risks to the fetus.

Nursing Mothers

It is not known whether this drug is excreted present in human milk. Because many drugs are excreted present in human milk, caution should be exercised when 3% Sodium Chloride Injection is administered to a nursing woman.

Pediatric Use

The use of 3% Sodium Chloride Injection in pediatric patients is based on clinical practice (see DOSAGE AND ADMINISTRATION).

Plasma electrolyte concentrations should be closely monitored in the pediatric population as this population may have impaired ability to regulate fluids and electrolytes.

Geriatric Use

Clinical studies of 3% Sodium Chloride Injection did not include sufficient numbers of subjects aged 65 and over to determine whether they respond differently from younger subjects. Other reported clinical experience has not identified differences in responses between the elderly and younger patients. In general, dose selection for an elderly patient should be cautious, usually starting at the low end of the dosing range, reflecting the greater frequency of decreased hepatic, renal, or cardiac function, and of concomitant disease or other drug therapy.

This drug is known to be substantially excreted by the kidney, and the risk of toxic reactions to this drug may be greater in patients with impaired renal function. Because elderly patients are more likely to have decreased renal function, care should be taken in dose selection, and it may be useful to monitor renal function.

ADVERSE REACTIONS:

Post-Marketing Adverse Reactions

The following adverse reactions have not been reported with 3% Sodium Chloride Injection but may occur:

- hyperchloremia
- hyperchloremic metabolic acidosis,
- hypersensitivity/infusion reactions, including hypotension, pyrexia, tremor, chills, urticaria, rash, and pruritus,
- Infusion site reactions, such as thrombosis, phlebitis, irritation, infusion site erythema, injection site streaking, burning sensation, infusion site urticaria.

If an adverse reaction does occur, discontinue the infusion, evaluate the patient, institute appropriate therapeutic countermeasures, and save the remainder of the fluid for examination if deemed necessary.

OVERDOSAGE:

Excessive administration of 3% Sodium Chloride Injection may lead to hypernatremia (which can lead to CNS manifestations, including seizures, coma, cerebral edema and death) and sodium overload (which can lead to central and/or peripheral edema).

When assessing an overdose, any additives in the solution must also be considered. The effects of an overdose may require immediate medical attention and treatment.

DOSAGE AND ADMINISTRATION:

As directed by a physician. Dosage, rate, and duration of administration are to be individualized and depend upon the indication for use, the patient's age, weight, clinical condition, concomitant treatment, and on the patient's clinical and laboratory response to treatment.

Parenteral drug products should be inspected visually for particulate matter and discoloration prior to administration whenever solution and container permit. Use of a final filter is recommended during administration of all parenteral solutions, where possible.

Do not administer unless solution is clear and seal is intact.

All injections in flexible plastic containers are intended for intravenous administration using sterile and nonpyrogenic equipment.

Additives may be incompatible. Complete information is not available. Those additives known to be incompatible should not be used. Consult with pharmacist, if available. If, in the informed judgment of the physician, it is deemed advisable to introduce additives, use aseptic technique. Mix thoroughly when additives have been introduced. Do not store solutions containing additives.

After opening the container, the contents should be used immediately and should not be stored for a subsequent infusion. Do not reconnect any partially used containers. Discard any unused portion.

HOW SUPPLIED:

3% Sodium Chloride Injection, USP in a single dose flexible plastic container, is available as follows:

Product No. | 530175 | 530175
Presentation | Single-Dose Container | Carton
NDC # | 63323-530-21 | 63323-530-75
Description | 15 grams per 500 mL in a 500 mL bag (30 mg per mL) | 20 Single-Dose Containers in 1 Carton

Exposure of pharmaceutical products to heat should be minimized. Avoid excessive heat.

STORAGE AND HANDLING

Store at 20° to 25°C (68° to 77°F) [see USP Controlled Room Temperature]; brief exposure up to 40°C/104°F does not adversely affect the product.

The container closure is not made with natural rubber latex. Non-PVC, Non-DEHP, Sterile.

INSTRUCTIONS FOR USE:

Check flexible container solution composition, lot number, and expiry date.

Do not remove solution container from its overwrap until immediately before use.

Use sterile equipment and aseptic technique.

To Open

1. Turn solution container over so that the text is face down. Using the pre-cut corner tabs, peel open the overwrap and remove solution container.
2. Check the solution container for leaks by squeezing firmly. If leaks are found, or if the seal is not intact, discard the solution.
3. Do not use if the solution is cloudy or a precipitate is present.

To Add Medication

1. Identify WHITE Additive Port with arrow pointing toward container.
2. Immediately before injecting additives, break off WHITE Additive Port Cap with the arrow pointing toward container.
3. Hold base of WHITE Additive Port horizontally.
4. Insert needle horizontally through the center of WHITE Additive Port's septum and inject additives.
5. Mix container contents thoroughly.

Preparation for Administration

1. Immediately before inserting the infusion set, break off BLUE Infusion Port Cap with the arrow pointing away from container.
2. Use a non-vented infusion set or close the air-inlet on a vented set.
3. Close the roller clamp of the infusion set.
4. Hold the base of BLUE Infusion Port.
5. Insert spike through BLUE Infusion Port by rotating wrist slightly until the spike is inserted. NOTE: See full directions accompanying administration set.

WARNING: Do not use flexible container in series connections.

Manufactured for:

Lake Zurich, IL 60047

Made in Germany

www.fresenius-kabi.com/us

451532A

Revised: February 2020

PACKAGE LABEL - PRINCIPAL DISPLAY – 3% Sodium Chloride Injection, USP 500 mL Bag Label

NDC 63323-530-21

freeflex®

500 mL

3% Sodium Chloride Injection, USP

15 grams per 500 mL (30 mg per mL)

Hypertonic Saline

For intravenous use. Rx only

PACKAGE LABEL - PRINCIPAL DISPLAY – 3% Sodium Chloride Injection, USP Case Label

NDC 63323-530-75 530175
3% Sodium Chloride Injection, USP,

15 grams per 500 mL

500 mL x 20 Single-Dose Container

Hypertonic Saline

For Intravenous Use

Rx only